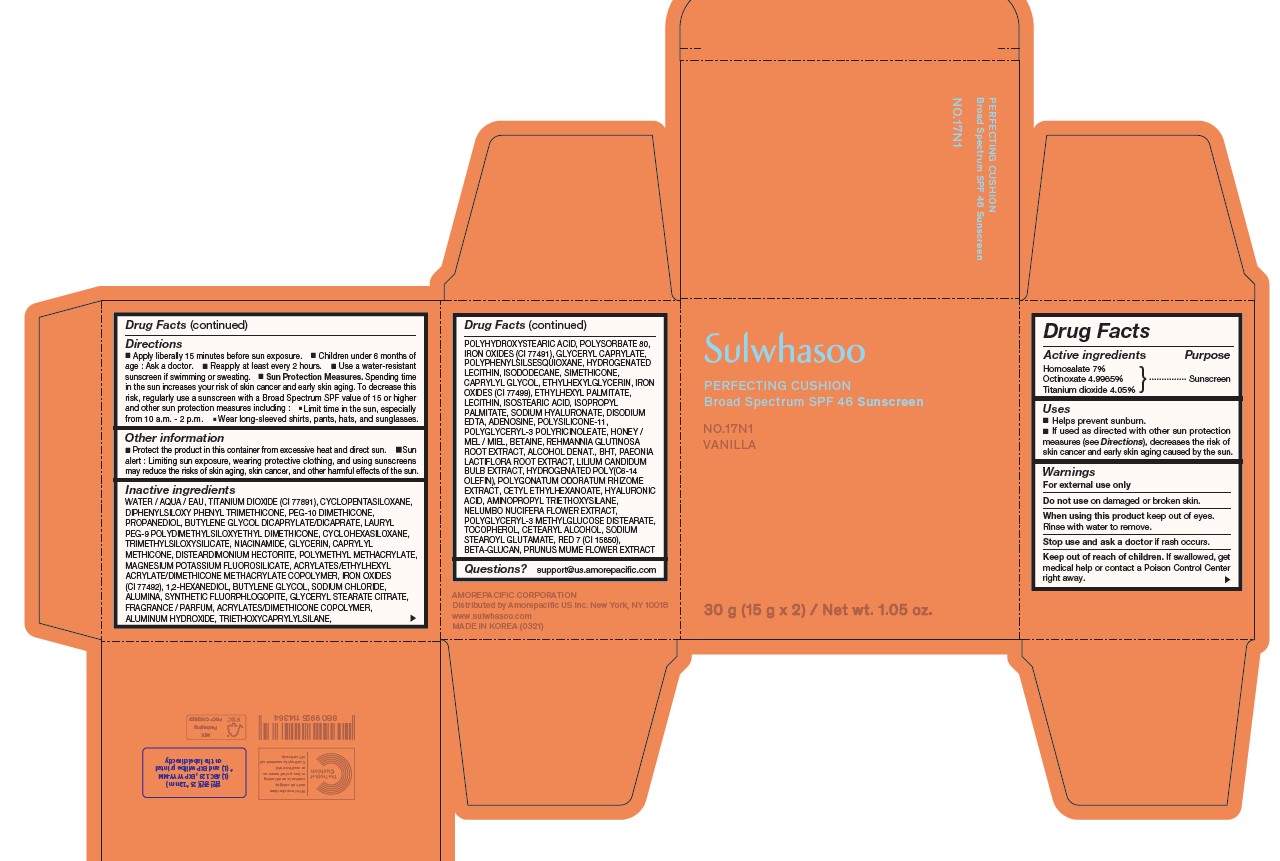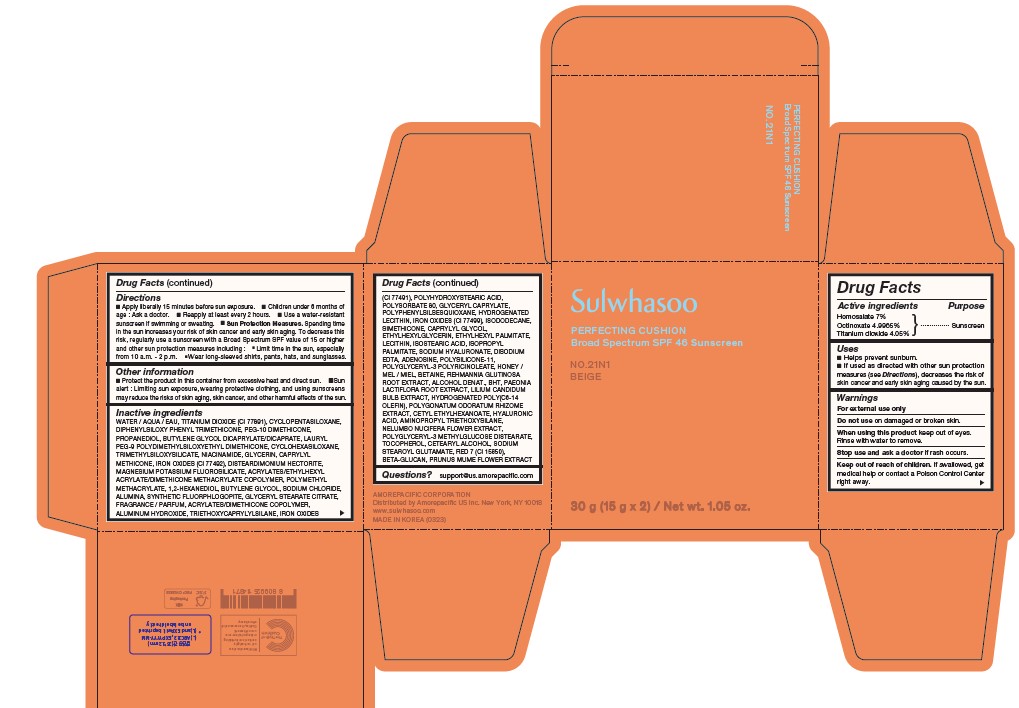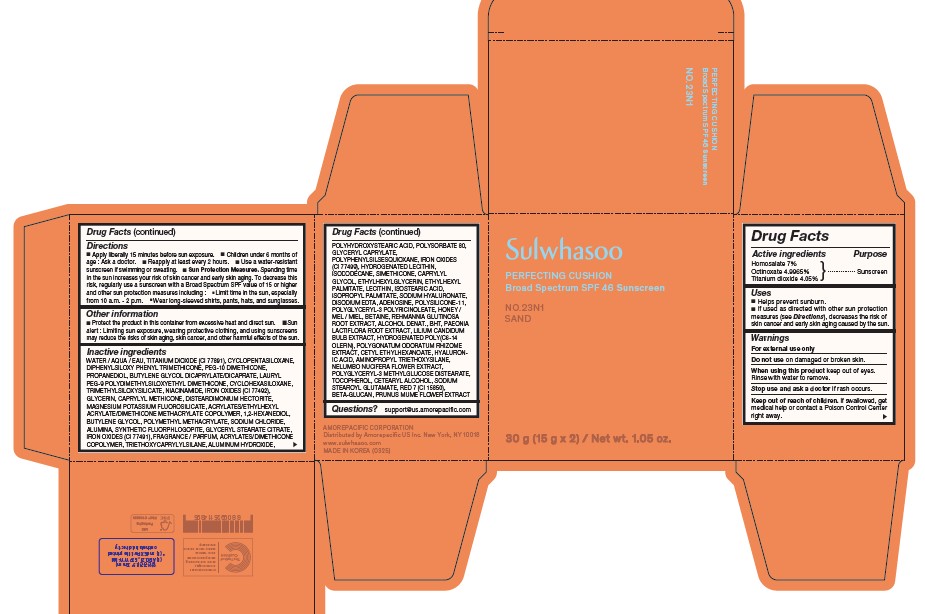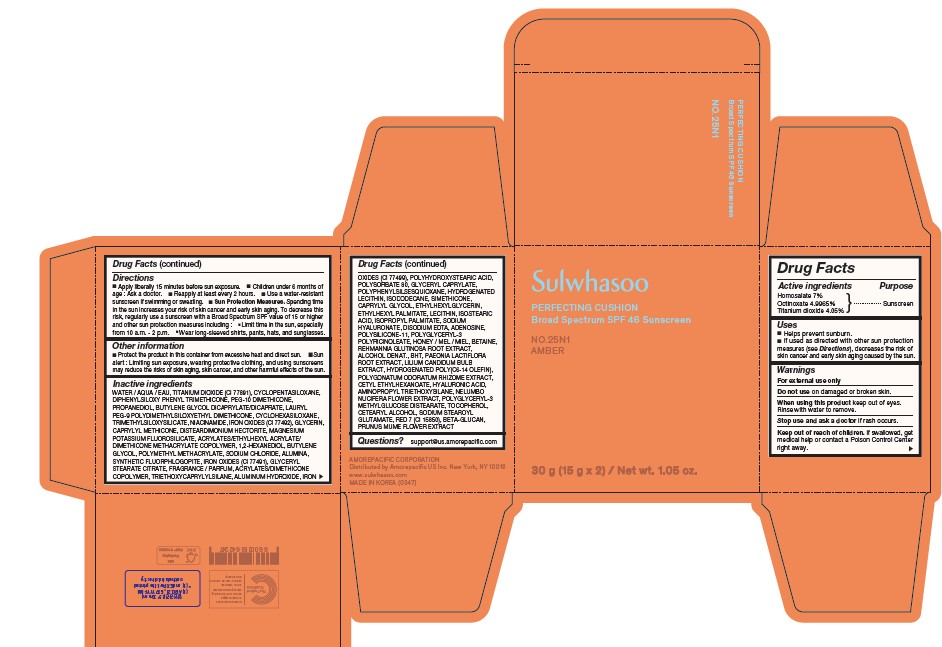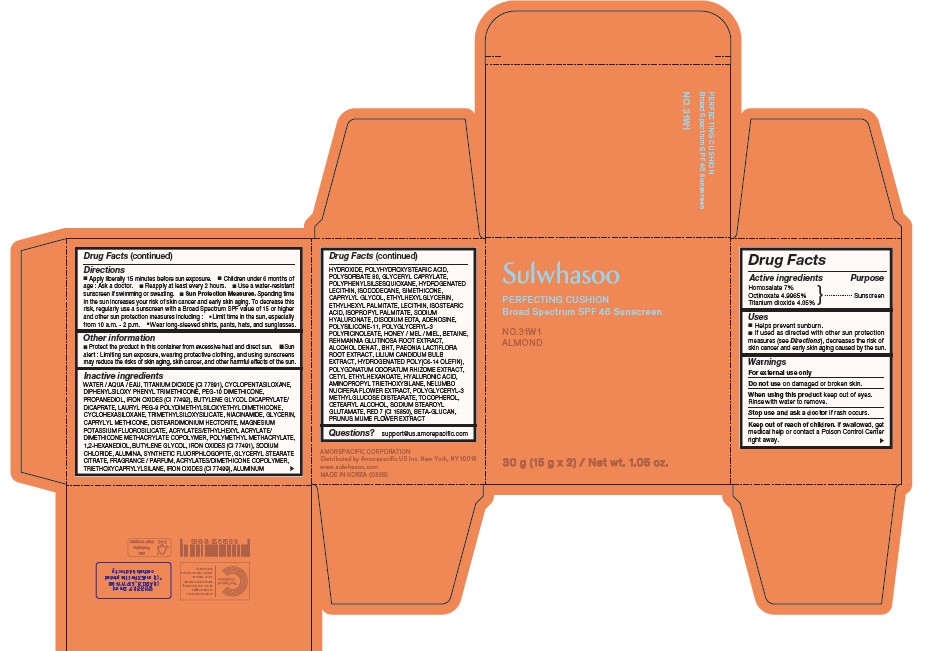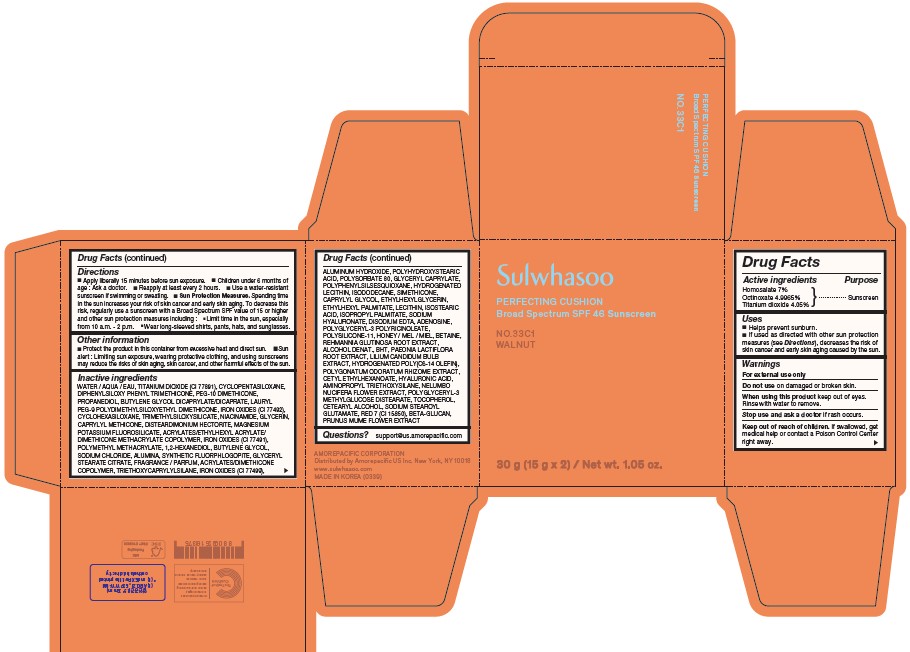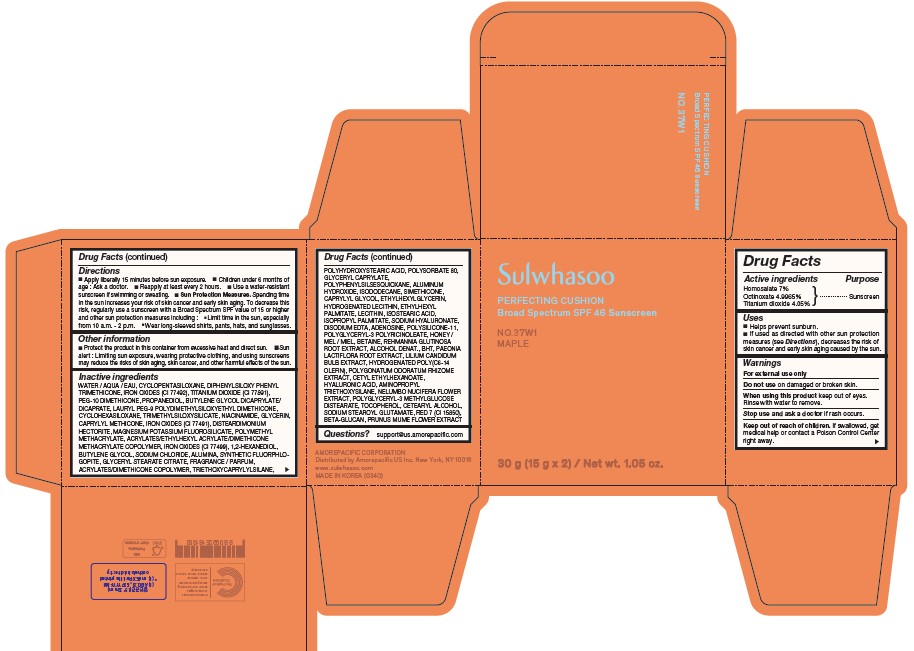 DRUG LABEL: Sulwhasoo Perfecting Cushion NO.37W1 Maple
NDC: 43419-093 | Form: LOTION
Manufacturer: Amorepacific Corporation
Category: otc | Type: HUMAN OTC DRUG LABEL
Date: 20250421

ACTIVE INGREDIENTS: HOMOSALATE 1.05 g/15 g; OCTINOXATE 0.749475 g/15 g; TITANIUM DIOXIDE 0.6075 g/15 g
INACTIVE INGREDIENTS: BUTYLENE GLYCOL DICAPRYLATE/DICAPRATE; TRIMETHYLSILOXYSILICATE (M/Q 0.6-0.8); GLYCERIN; 1,2-HEXANEDIOL; SODIUM CHLORIDE; ALUMINUM HYDROXIDE; CI 77491; HYDROGENATED SOYBEAN LECITHIN; CAPRYLYL GLYCOL; CI 77499; SODIUM HYALURONATE; POLYGLYCERYL-3 PENTARICINOLEATE; PAEONIA LACTIFLORA ROOT; PEG-10 DIMETHICONE (200 CST); NIACINAMIDE; POLYSORBATE 80; ISOSTEARIC ACID; HYALURONIC ACID; NELUMBO NUCIFERA FLOWER; GLYCERYL STEARATE CITRATE; BHT; CAPRYLYL METHICONE; DISTEARDIMONIUM HECTORITE; POLY(METHYL METHACRYLATE; 450000 MW); BUTYLENE GLYCOL; MAGNESIUM POTASSIUM ALUMINOSILICATE FLUORIDE; CI 15850; CYCLOPENTASILOXANE; DIPHENYLSILOXY PHENYL TRIMETHICONE; GLYCERYL CAPRYLATE; DIMETHICONE/VINYL DIMETHICONE CROSSPOLYMER (SOFT PARTICLE); REHMANNIA GLUTINOSA ROOT; CETEARYL ALCOHOL; SODIUM CARBOXYMETHYL .BETA.-GLUCAN (DS 0.65-0.85); LAURYL PEG-9 POLYDIMETHYLSILOXYETHYL DIMETHICONE; POLYPHENYLSILSESQUIOXANE (RI 1.55); DIMETHICONOL/TRIMETHYLSILOXYSILICATE CROSSPOLYMER (40/60 W/W; 1000000 PA.S); ETHYLHEXYLGLYCERIN; HYDROGENATED POLY(C6-14 OLEFIN; 6 CST); POLYGLYCERYL-3 METHYLGLUCOSE DISTEARATE; POLYHYDROXYSTEARIC ACID (2300 MW); ADENOSINE; EDETATE DISODIUM; ETHYLHEXYL PALMITATE; ISOPROPYL PALMITATE; LILIUM CANDIDUM BULB; CETYL ETHYLHEXANOATE; CI 77492; ALUMINA; TRIETHOXYCAPRYLYLSILANE; TOCOPHEROL; AMINOPROPYL TRIETHOXYSILANE; DEHYDRATED ALCOHOL; PROPANEDIOL; CYCLOHEXASILOXANE; SODIUM STEAROYL GLUTAMATE; PRUNUS MUME FLOWER; HONEY; BETAINE; WATER; 2-ETHYLHEXYL ACRYLATE, METHACRYLATE, METHYL METHACRYLATE, OR BUTYL METHACRYLATE/HYDROXYPROPYL DIMETHICONE COPOLYMER (30000-300000 MW); ISODODECANE

SULWHASOO PERFECTING CUSHION Broad Spectrum SPF 46

Drug Facts

ACTIVE INGREDIENTS

Homosalate 7%
Octinoxate 4.9965%
Titanium dioxide 4.05%

PURPOSE

Sunscreen

USES

◼ Helps prevent sunburn.
◼ If used as directed with other sun protection measures (see Directions), decreases the risk of skin cancer and early skin aging caused by the sun.

WARNINGS

- For external use only

- Do not use on broken skin.

- When using this product avoid contact with eyes. If contact occurs, rinse thoroughly with water.

- Stop use and ask a doctor if rash occurs.

- Keep out of reach of children. If swallowed, call a poison control centre or get medical help right away.

DIRECTIONS

◼ Apply liberally 15 minutes before sun exposure.

◼ Children under 6 months of age : Ask a doctor.

◼ Reapply at least every 2 hours.

◼ Use a water-resistant sunscreen if swimming or sweating.

◼ Sun Protection Measures. Spending time in the sun increases your risk of skin cancer and early skin aging. To decrease this
risk, regularly use a sunscreen with a Broad Spectrum SPF value of 15 or higher and other sun protection measures including :

- Limit time in the sun, especially from 10 a.m. - 2 p.m.
- Wear long-sleeved shirts, pants, hats, and sunglasses.

OTHER INFORMATION

- Protect the product in this container from excessive heat and direct sun.
- Sun alert : Limiting sun exposure, wearing protective clothing, and using sunscreens may reduce the risks of skin aging, skin cancer, and other harmful effects of the sun.

INACTIVE INGREDIENTS

17N1 | WATER / AQUA / EAU, TITANIUM DIOXIDE (CI 77891), CYCLOPENTASILOXANE, DIPHENYLSILOXY PHENYL TRIMETHICONE, PEG-10 DIMETHICONE, PROPANEDIOL, BUTYLENE GLYCOL DICAPRYLATE/DICAPRATE, LAURYL PEG-9 POLYDIMETHYLSILOXYETHYL DIMETHICONE, CYCLOHEXASILOXANE, TRIMETHYLSILOXYSILICATE, NIACINAMIDE, GLYCERIN, CAPRYLYL METHICONE, DISTEARDIMONIUM HECTORITE, POLYMETHYL METHACRYLATE, MAGNESIUM POTASSIUM FLUOROSILICATE, ACRYLATES/ETHYLHEXYL ACRYLATE/DIMETHICONE METHACRYLATE COPOLYMER, IRON OXIDES (CI 77492), 1,2-HEXANEDIOL, BUTYLENE GLYCOL, SODIUM CHLORIDE, ALUMINA, SYNTHETIC FLUORPHLOGOPITE, GLYCERYL STEARATE CITRATE, FRAGRANCE / PARFUM, ACRYLATES/DIMETHICONE COPOLYMER, ALUMINUM HYDROXIDE, TRIETHOXYCAPRYLYLSILANE, POLYHYDROXYSTEARIC ACID, POLYSORBATE 80, IRON OXIDES (CI 77491), GLYCERYL CAPRYLATE, POLYPHENYLSILSESQUIOXANE, HYDROGENATED LECITHIN, ISODODECANE, SIMETHICONE, CAPRYLYL GLYCOL, ETHYLHEXYLGLYCERIN, IRON OXIDES (CI 77499), ETHYLHEXYL PALMITATE, LECITHIN, ISOSTEARIC ACID, ISOPROPYL PALMITATE, SODIUM HYALURONATE, DISODIUM EDTA, ADENOSINE, POLYSILICONE-11, POLYGLYCERYL-3 POLYRICINOLEATE, HONEY / MEL / MIEL, BETAINE, REHMANNIA GLUTINOSA ROOT EXTRACT, ALCOHOL DENAT., BHT, PAEONIA LACTIFLORA ROOT EXTRACT, LILIUM CANDIDUM BULB EXTRACT, HYDROGENATED POLY(C6-14 OLEFIN), POLYGONATUM ODORATUM RHIZOME EXTRACT, CETYL ETHYLHEXANOATE, HYALURONIC ACID, AMINOPROPYL TRIETHOXYSILANE, NELUMBO NUCIFERA FLOWER EXTRACT, POLYGLYCERYL-3 METHYLGLUCOSE DISTEARATE, TOCOPHEROL, CETEARYL ALCOHOL, SODIUM STEAROYL GLUTAMATE, RED 7 (CI 15850), BETA-GLUCAN, PRUNUS MUME FLOWER EXTRACT
21N1 | WATER / AQUA / EAU, TITANIUM DIOXIDE (CI 77891), CYCLOPENTASILOXANE, DIPHENYLSILOXY PHENYL TRIMETHICONE, PEG-10 DIMETHICONE, PROPANEDIOL, BUTYLENE GLYCOL DICAPRYLATE/DICAPRATE, LAURYL PEG-9 POLYDIMETHYLSILOXYETHYL DIMETHICONE, CYCLOHEXASILOXANE, TRIMETHYLSILOXYSILICATE, NIACINAMIDE, GLYCERIN, CAPRYLYL METHICONE, IRON OXIDES (CI 77492), DISTEARDIMONIUM HECTORITE, MAGNESIUM POTASSIUM FLUOROSILICATE, ACRYLATES/ETHYLHEXYL ACRYLATE/ DIMETHICONE METHACRYLATE COPOLYMER, POLYMETHYL METHACRYLATE, 1,2-HEXANEDIOL, BUTYLENE GLYCOL, SODIUM CHLORIDE, ALUMINA, SYNTHETIC FLUORPHLOGOPITE, GLYCERYL STEARATE CITRATE, FRAGRANCE / PARFUM, ACRYLATES/DIMETHICONE COPOLYMER, ALUMINUM HYDROXIDE, TRIETHOXYCAPRYLYLSILANE, IRON OXIDES (CI 77491), POLYHYDROXYSTEARIC ACID, POLYSORBATE 80, GLYCERYL CAPRYLATE, POLYPHENYLSILSESQUIOXANE, HYDROGENATED LECITHIN, IRON OXIDES (CI 77499), ISODODECANE, SIMETHICONE, CAPRYLYL GLYCOL, ETHYLHEXYLGLYCERIN, ETHYLHEXYL PALMITATE, LECITHIN, ISOSTEARIC ACID, ISOPROPYL PALMITATE, SODIUM HYALURONATE, DISODIUM EDTA, ADENOSINE, POLYSILICONE-11, POLYGLYCERYL-3 POLYRICINOLEATE, HONEY / MEL / MIEL, BETAINE, REHMANNIA GLUTINOSA ROOT EXTRACT, ALCOHOL DENAT., BHT, PAEONIA LACTIFLORA ROOT EXTRACT, LILIUM CANDIDUM BULB EXTRACT, HYDROGENATED POLY(C6-14 OLEFIN), POLYGONATUM ODORATUM RHIZOME EXTRACT, CETYL ETHYLHEXANOATE, HYALURONIC ACID, AMINOPROPYL TRIETHOXYSILANE, NELUMBO NUCIFERA FLOWER EXTRACT, POLYGLYCERYL-3 METHYLGLUCOSE DISTEARATE, TOCOPHEROL, CETEARYL ALCOHOL, SODIUM STEAROYL GLUTAMATE, RED 7 (CI 15850), BETA-GLUCAN, PRUNUS MUME FLOWER EXTRACT
23N1 | WATER / AQUA / EAU, TITANIUM DIOXIDE (CI 77891), CYCLOPENTASILOXANE, DIPHENYLSILOXY PHENYL TRIMETHICONE, PEG-10 DIMETHICONE, PROPANEDIOL, BUTYLENE GLYCOL DICAPRYLATE/DICAPRATE, LAURYL PEG-9 POLYDIMETHYLSILOXYETHYL DIMETHICONE, CYCLOHEXASILOXANE, TRIMETHYLSILOXYSILICATE, NIACINAMIDE, IRON OXIDES (CI 77492), GLYCERIN, CAPRYLYL METHICONE, DISTEARDIMONIUM HECTORITE, MAGNESIUM POTASSIUM FLUOROSILICATE, ACRYLATES/ETHYLHEXYL ACRYLATE/ DIMETHICONE METHACRYLATE COPOLYMER, 1,2-HEXANEDIOL, BUTYLENE GLYCOL, POLYMETHYL METHACRYLATE, SODIUM CHLORIDE, ALUMINA, SYNTHETIC FLUORPHLOGOPITE, GLYCERYL STEARATE CITRATE, IRON OXIDES (CI 77491), FRAGRANCE / PARFUM, ACRYLATES/DIMETHICONE COPOLYMER, TRIETHOXYCAPRYLYLSILANE, ALUMINUM HYDROXIDE, POLYHYDROXYSTEARIC ACID, POLYSORBATE 80, GLYCERYL CAPRYLATE, POLYPHENYLSILSESQUIOXANE, IRON OXIDES (CI 77499), HYDROGENATED LECITHIN, ISODODECANE, SIMETHICONE, CAPRYLYL GLYCOL, ETHYLHEXYLGLYCERIN, ETHYLHEXYL PALMITATE, LECITHIN, ISOSTEARIC ACID, ISOPROPYL PALMITATE, SODIUM HYALURONATE, DISODIUM EDTA, ADENOSINE, POLYSILICONE-11, POLYGLYCERYL-3 POLYRICINOLEATE, HONEY / MEL / MIEL, BETAINE, REHMANNIA GLUTINOSA ROOT EXTRACT, ALCOHOL DENAT., BHT, PAEONIA LACTIFLORA ROOT EXTRACT, LILIUM CANDIDUM BULB EXTRACT, HYDROGENATED POLY(C6-14 OLEFIN), POLYGONATUM ODORATUM RHIZOME EXTRACT, CETYL ETHYLHEXANOATE, HYALURONIC ACID, AMINOPROPYL TRIETHOXYSILANE, NELUMBO NUCIFERA FLOWER EXTRACT, POLYGLYCERYL-3 METHYLGLUCOSE DISTEARATE, TOCOPHEROL, CETEARYL ALCOHOL, SODIUM STEAROYL GLUTAMATE, RED 7 (CI 15850), BETA-GLUCAN, PRUNUS MUME FLOWER EXTRACT
25N1 | WATER / AQUA / EAU, TITANIUM DIOXIDE (CI 77891), CYCLOPENTASILOXANE, DIPHENYLSILOXY PHENYL TRIMETHICONE, PEG-10 DIMETHICONE, PROPANEDIOL, BUTYLENE GLYCOL DICAPRYLATE/DICAPRATE, LAURYL PEG-9 POLYDIMETHYLSILOXYETHYL DIMETHICONE, CYCLOHEXASILOXANE, TRIMETHYLSILOXYSILICATE, NIACINAMIDE, IRON OXIDES (CI 77492), GLYCERIN, CAPRYLYL METHICONE, DISTEARDIMONIUM HECTORITE, MAGNESIUM POTASSIUM FLUOROSILICATE, ACRYLATES/ETHYLHEXYL ACRYLATE/ DIMETHICONE METHACRYLATE COPOLYMER, 1,2-HEXANEDIOL, BUTYLENE GLYCOL, POLYMETHYL METHACRYLATE, SODIUM CHLORIDE, ALUMINA, SYNTHETIC FLUORPHLOGOPITE, IRON OXIDES (CI 77491), GLYCERYL STEARATE CITRATE, FRAGRANCE / PARFUM, ACRYLATES/DIMETHICONE COPOLYMER, TRIETHOXYCAPRYLYLSILANE, ALUMINUM HYDROXIDE, IRON OXIDES (CI 77499), POLYHYDROXYSTEARIC ACID, POLYSORBATE 80, GLYCERYL CAPRYLATE, POLYPHENYLSILSESQUIOXANE, HYDROGENATED LECITHIN, ISODODECANE, SIMETHICONE, CAPRYLYL GLYCOL, ETHYLHEXYLGLYCERIN, ETHYLHEXYL PALMITATE, LECITHIN, ISOSTEARIC ACID, ISOPROPYL PALMITATE, SODIUM HYALURONATE, DISODIUM EDTA, ADENOSINE, POLYSILICONE-11, POLYGLYCERYL-3 POLYRICINOLEATE, HONEY / MEL / MIEL, BETAINE, REHMANNIA GLUTINOSA ROOT EXTRACT, ALCOHOL DENAT., BHT, PAEONIA LACTIFLORA ROOT EXTRACT, LILIUM CANDIDUM BULB EXTRACT, HYDROGENATED POLY(C6-14 OLEFIN), POLYGONATUM ODORATUM RHIZOME EXTRACT, CETYL ETHYLHEXANOATE, HYALURONIC ACID, AMINOPROPYL TRIETHOXYSILANE, NELUMBO NUCIFERA FLOWER EXTRACT, POLYGLYCERYL-3 METHYLGLUCOSE DISTEARATE, TOCOPHEROL, CETEARYL ALCOHOL, SODIUM STEAROYL GLUTAMATE, RED 7 (CI 15850), BETA-GLUCAN, PRUNUS MUME FLOWER EXTRACT
31N1 | WATER / AQUA / EAU, TITANIUM DIOXIDE (CI 77891), CYCLOPENTASILOXANE, DIPHENYLSILOXY PHENYL TRIMETHICONE, PEG-10 DIMETHICONE, PROPANEDIOL, IRON OXIDES (CI 77492), BUTYLENE GLYCOL DICAPRYLATE/ DICAPRATE, LAURYL PEG-9 POLYDIMETHYLSILOXYETHYL DIMETHICONE, CYCLOHEXASILOXANE, TRIMETHYLSILOXYSILICATE, NIACINAMIDE, GLYCERIN, CAPRYLYL METHICONE, DISTEARDIMONIUM HECTORITE, MAGNESIUM POTASSIUM FLUOROSILICATE, ACRYLATES/ETHYLHEXYL ACRYLATE/DI METHICONE METHACRYLATE COPOLYMER, POLYMETHYL METHACRYLATE, 1,2-HEXANEDIOL, BUTYLENE GLYCOL, IRON OXIDES (CI 77491), SODIUM CHLORIDE, ALUMINA, SYNTHETIC FLUORPHLOGOPITE, GLYCERYL STEARATE CITRATE, FRAGRANCE / PARFUM, ACRYLATES/DIMETHICONE COPOLYMER, TRIETHOXYCAPRYLYLSILANE, IRON OXIDES (CI 77499), ALUMINUM HYDROXIDE, POLYHYDROXYSTEARIC ACID, POLYSORBATE 80, GLYCERYL CAPRYLATE, POLYPHENYLSILSESQUIOXANE, HYDROGENATED LECITHIN, ISODODECANE, SIMETHICONE, CAPRYLYL GLYCOL, ETHYLHEXYLGLYCERIN, ETHYLHEXYL PALMITATE, LECITHIN, ISOSTEARIC ACID, ISOPROPYL PALMITATE, SODIUM HYALURONATE, DISODIUM EDTA, ADENOSINE, POLYSILICONE-11, POLYGLYCERYL-3 POLYRICINOLEATE, HONEY / MEL / MIEL, BETAINE, REHMANNIA GLUTINOSA ROOT EXTRACT, ALCOHOL DENAT., BHT, PAEONIA LACTIFLORA ROOT EXTRACT, LILIUM CANDIDUM BULB EXTRACT, HYDROGENATED POLY(C6-14 OLEFIN), POLYGONATUM ODORATUM RHIZOME EXTRACT, CETYL ETHYLHEXANOATE, HYALURONIC ACID, AMINOPROPYL TRIETHOXYSILANE, NELUMBO NUCIFERA FLOWER EXTRACT, POLYGLYCERYL-3 METHYLGLUCOSE DISTEARATE, TOCOPHEROL, CETEARYL ALCOHOL, SODIUM STEAROYL GLUTAMATE, RED 7 (CI 15850), BETA-GLUCAN, PRUNUS MUME FLOWER EXTRACT
33C1 | WATER / AQUA / EAU, TITANIUM DIOXIDE (CI 77891), CYCLOPENTASILOXANE, DIPHENYLSILOXY PHENYL TRIMETHICONE, PEG-10 DIMETHICONE, PROPANEDIOL, BUTYLENE GLYCOL DICAPRYLATE/DICAPRATE, LAURYL PEG-9 POLYDIMETHYLSILOXYETHYL DIMETHICONE, IRON OXIDES (CI 77492), CYCLOHEXASILOXANE, TRIMETHYLSILOXYSILICATE, NIACINAMIDE, GLYCERIN, CAPRYLYL METHICONE, DISTEARDIMONIUM HECTORITE, MAGNESIUM POTASSIUM FLUOROSILICATE, ACRYLATES/ETHYLHEXYL ACRYLATE/ DIMETHICONE METHACRYLATE COPOLYMER, IRON OXIDES (CI 77491), POLYMETHYL METHACRYLATE, 1,2-HEXANEDIOL, BUTYLENE GLYCOL, SODIUM CHLORIDE, ALUMINA, SYNTHETIC FLUORPHLOGOPITE, GLYCERYL STEARATE CITRATE, FRAGRANCE / PARFUM, ACRYLATES/DIMETHICONE COPOLYMER, TRIETHOXYCAPRYLYLSILANE, IRON OXIDES (CI 77499), ALUMINUM HYDROXIDE, POLYHYDROXYSTEARIC ACID, POLYSORBATE 80, GLYCERYL CAPRYLATE, POLYPHENYLSILSESQUIOXANE, HYDROGENATED LECITHIN, ISODODECANE, SIMETHICONE, CAPRYLYL GLYCOL, ETHYLHEXYLGLYCERIN, ETHYLHEXYL PALMITATE, LECITHIN, ISOSTEARIC ACID, ISOPROPYL PALMITATE, SODIUM HYALURONATE, DISODIUM EDTA, ADENOSINE, POLYGLYCERYL-3 POLYRICINOLEATE, POLYSILICONE-11, HONEY / MEL / MIEL, BETAINE, REHMANNIA GLUTINOSA ROOT EXTRACT, ALCOHOL DENAT., BHT, PAEONIA LACTIFLORA ROOT EXTRACT, LILIUM CANDIDUM BULB EXTRACT, HYDROGENATED POLY(C6-14 OLEFIN), POLYGONATUM ODORATUM RHIZOME EXTRACT, CETYL ETHYLHEXANOATE, HYALURONIC ACID, AMINOPROPYL TRIETHOXYSILANE, NELUMBO NUCIFERA FLOWER EXTRACT, POLYGLYCERYL-3 METHYLGLUCOSE DISTEARATE, TOCOPHEROL, CETEARYL ALCOHOL, SODIUM STEAROYL GLUTAMATE, RED 7 (CI 15850), BETA-GLUCAN, PRUNUS MUME FLOWER EXTRACT
37W1 | WATER / AQUA / EAU, CYCLOPENTASILOXANE, DIPHENYLSILOXY PHENYL TRIMETHICONE, IRON OXIDES (CI 77492), TITANIUM DIOXIDE (CI 77891), PEG-10 DIMETHICONE, PROPANEDIOL, BUTYLENE GLYCOL DICAPRYLATE/DICAPRATE, LAURYL PEG-9 POLYDIMETHYLSILOXYETHYL DIMETHICONE, CYCLOHEXASILOXANE, TRIMETHYLSILOXYSILICATE, NIACINAMIDE, GLYCERIN, CAPRYLYL METHICONE, IRON OXIDES (CI 77491), DISTEARDIMONIUM HECTORITE, MAGNESIUM POTASSIUM FLUOROSILICATE, POLYMETHYL METHACRYLATE, ACRYLATES/ETHYLHEXYL ACRYLATE/DIMETHICONE METHACRYLATE COPOLYMER, IRON OXIDES (CI 77499), 1,2-HEXANEDIOL, BUTYLENE GLYCOL, SODIUM CHLORIDE, ALUMINA, SYNTHETIC FLUORPHLOGOPITE, GLYCERYL STEARATE CITRATE, FRAGRANCE / PARFUM, ACRYLATES/DIMETHICONE COPOLYMER, TRIETHOXYCAPRYLYLSILANE, POLYHYDROXYSTEARIC ACID, POLYSORBATE 80, GLYCERYL CAPRYLATE, POLYPHENYLSILSESQUIOXANE, ALUMINUM HYDROXIDE, ISODODECANE, SIMETHICONE, CAPRYLYL GLYCOL, ETHYLHEXYLGLYCERIN, HYDROGENATED LECITHIN, ETHYLHEXYL PALMITATE, LECITHIN, ISOSTEARIC ACID, ISOPROPYL PALMITATE, SODIUM HYALURONATE, DISODIUM EDTA, ADENOSINE, POLYSILICONE-11, POLYGLYCERYL-3 POLYRICINOLEATE, HONEY / MEL / MIEL, BETAINE, REHMANNIA GLUTINOSA ROOT EXTRACT, ALCOHOL DENAT., BHT, PAEONIA LACTIFLORA ROOT EXTRACT, LILIUM CANDIDUM BULB EXTRACT, HYDROGENATED POLY(C6-14 OLEFIN), POLYGONATUM ODORATUM RHIZOME EXTRACT, CETYL ETHYLHEXANOATE, HYALURONIC ACID, AMINOPROPYL TRIETHOXYSILANE, NELUMBO NUCIFERA FLOWER EXTRACT, POLYGLYCERYL-3 METHYLGLUCOSE DISTEARATE, TOCOPHEROL, CETEARYL ALCOHOL, SODIUM STEAROYL GLUTAMATE, RED 7 (CI 15850), BETA-GLUCAN, PRUNUS MUME FLOWER EXTRACT